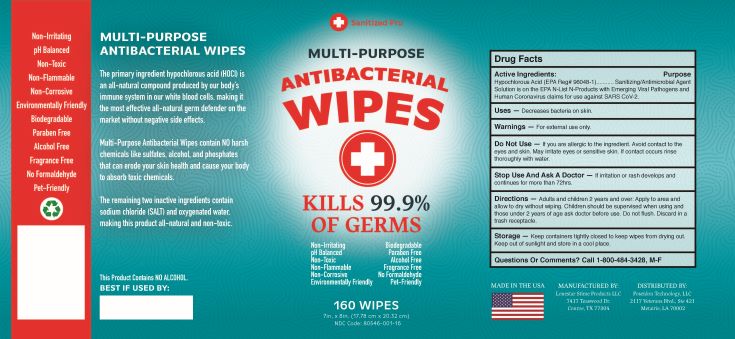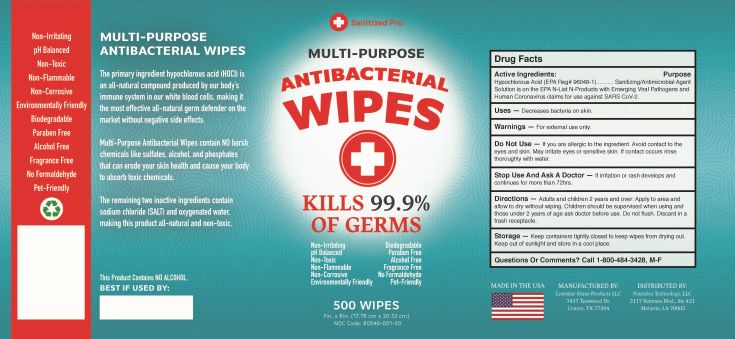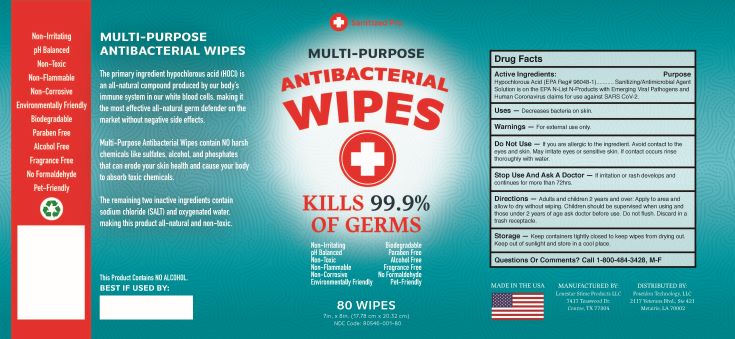 DRUG LABEL: Sanitized Pro Multi-Purpose Antibacterial Wipes
NDC: 80546-001 | Form: CLOTH
Manufacturer: Poseidon Technology, LLC
Category: otc | Type: HUMAN OTC DRUG LABEL
Date: 20200922

ACTIVE INGREDIENTS: HYPOCHLOROUS ACID 5 g/100 g
INACTIVE INGREDIENTS: WATER; SODIUM CHLORIDE 16.26 g/100 g

Multi-Purpose Antibacterial Wipes

1. Hypochlorous Acid
2. Sodium Chloride
3. Water.

Active Ingredient(s)

Hypochlorous Acid (EPA Reg# 96048-1)...........Sanitizing/Antimicrobial Agent
Solution is on the EPA N-List N-Products with Emerging Viral Pathogens and
Human Coronavirus claims for use against SARS CoV-2.

Purpose

Sanitizing/Antimicrobial Agent

Use

Decreases bacteria on skin.

Warnings

For external use only.

Do not use

If you are allergic to the ingredient. Avoid contact to the
eyes and skin. May irritate eyes or sensitive skin. If contact occurs rinse
thoroughly with water.

WHEN USING

Avoid contact of eyes and skin at full strength may irritate eyes or sensitive skin. In case of eye contact immediately flush eyes with plenty of fresh water. If skin irritation occurs, wash with soap and water.

STOP USE

If irritation or rash develops and
continues for more than 72hrs.

Keep out of reach of children. If swallowed, get medical help or contact a Poison Control Center right away.

Directions

Adults and children 2 years and over: Apply to area and
allow to dry without wiping. Children should be supervised when using and
those under 2 years of age ask doctor before use. Do not flush. Discard in a
trash receptacle.

Other information

Storage - Keep containers tightly closed to keep wipes from drying out.
Keep out of sunlight and store in a cool place.

Inactive ingredients

Water and Sodium Chloride

RECENT MAJOR CHANGES

Decreases bacteria on skin.